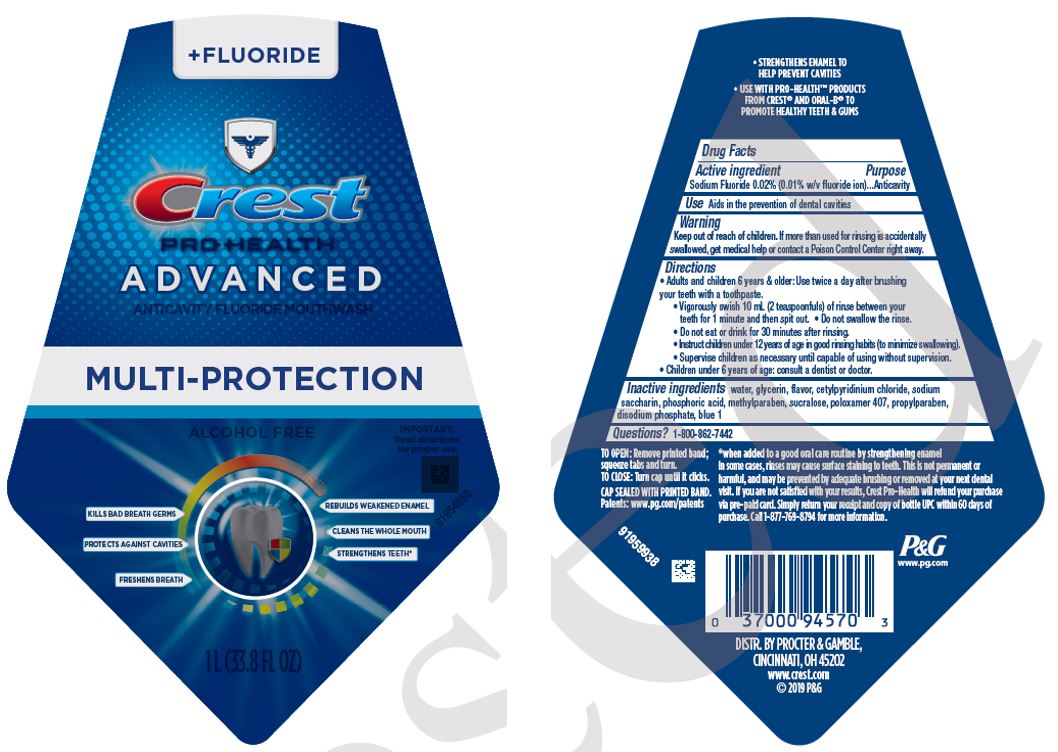 DRUG LABEL: Crest Pro-Health
NDC: 84126-600 | Form: RINSE
Manufacturer: The Procter & Gamble Manufacturing Company
Category: otc | Type: HUMAN OTC DRUG LABEL
Date: 20250806

ACTIVE INGREDIENTS: SODIUM FLUORIDE 0.1 mg/1 mL
INACTIVE INGREDIENTS: WATER; GLYCERIN; CETYLPYRIDINIUM CHLORIDE; SACCHARIN SODIUM; PHOSPHORIC ACID; METHYLPARABEN; SUCRALOSE; POLOXAMER 407; PROPYLPARABEN; SODIUM PHOSPHATE, DIBASIC, ANHYDROUS; FD&C BLUE NO. 1

Crest®Pro-Health™
Advanced Multi-Protection

Drug Facts

Active ingredient

Sodium Fluoride 0.02% (0.01% w/v fluoride ion)

Purpose

Anticavity

Use

Aids in the prevention of dental cavities

Warning

Keep out of reach of children.If more than used for rinsing is accidentally swallowed, get medical help or contact a Poison Control Center right away.

Directions

- Adults and children 6 years & older:
  - Use twice a day after brushing your teeth with a toothpaste.
  - Vigorously swish 10 mL (2 teaspoonfuls) of rinse between your teeth for 1 minute and then spit out.
  - Do not swallow the rinse.
  - Do not eat or drink for 30 minutes after rinsing.
  - Instruct children under 12 years of age in good rinsing habits (to minimize swallowing).
  - Supervise children as necessary until capable of using without supervision.
- Children under 6 years of age: consult a dentist or doctor.

Inactive ingredients

water, glycerin, flavor, poloxamer 407, cetylpyridinium chloride, sodium saccharin, phosphoric acid, methylparaben, sucralose, propylparaben, disodium phosphate, blue 1

Questions?

1-800-862-7442

DISTR. BY PROCTER & GAMBLE,
CINCINNATI, OH 45202

PRINCIPAL DISPLAY PANEL - 1 L Bottle Label

+ FLUORIDE

CREST

PRO-HEALTH

ADVANCED

ANTICAVITY FLUORIDE MOUTHWASH

MULTI-PROTECTION

ALCOHOL FREE

IMPORTANT:

Read directions

for proper use.

- KILLS BAD BREATH GERMS
- REBUILDS WEAKENED ENAMEL
- PROTECTS AGAINST CAVITIES
- CLEANS WHOLE MOUTH
- FRESHENS BREATH
- STRENGTHENS TEETH

1L 33.8 FL OZ)